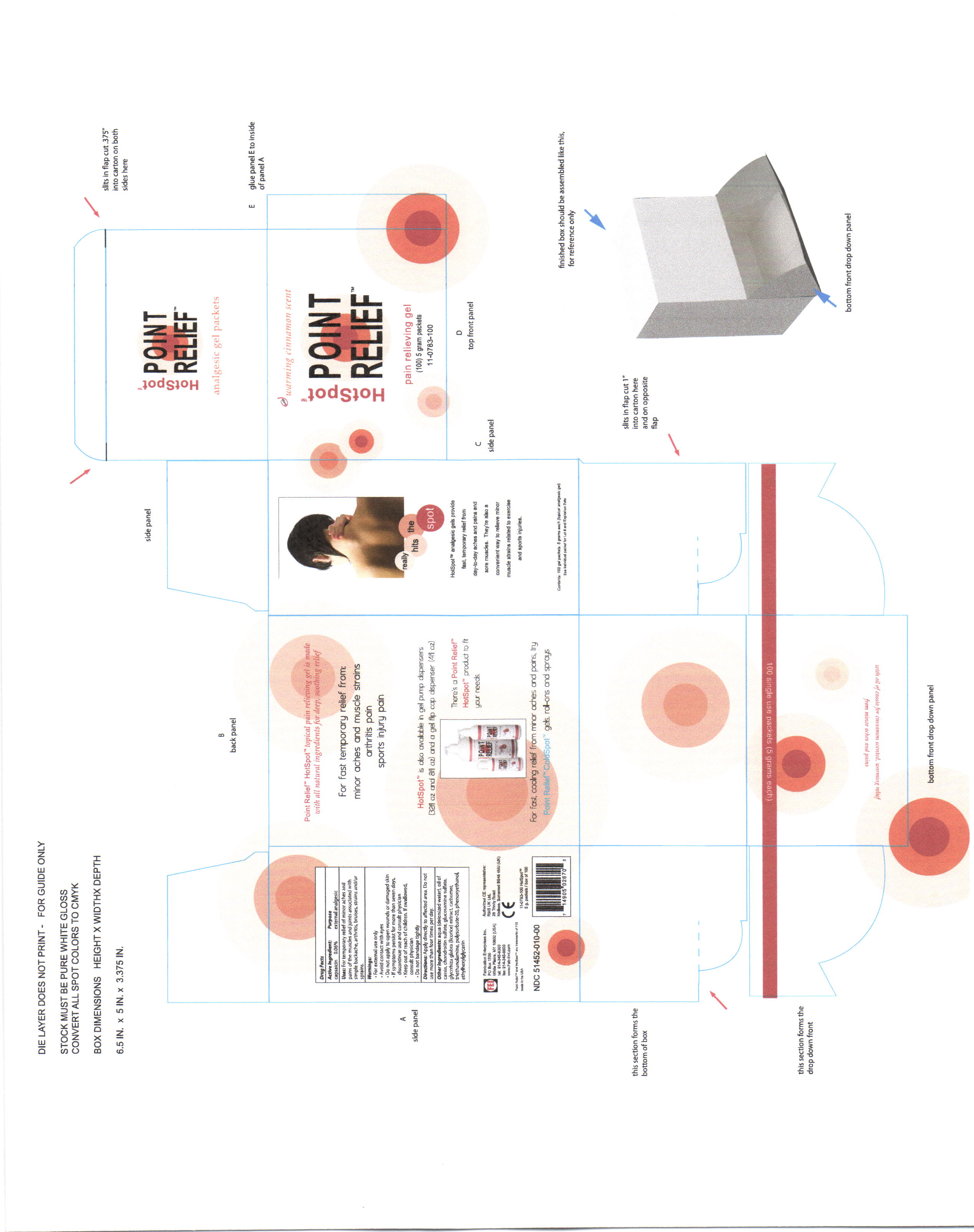 DRUG LABEL: Hot spot
NDC: 51452-010 | Form: GEL
Manufacturer: Fabrication Enterprises, inc.
Category: otc | Type: HUMAN OTC DRUG LABEL
Date: 20111013

ACTIVE INGREDIENTS: CAPSAICIN .03 mL/5 mL
INACTIVE INGREDIENTS: water; polysorbate 20; CHONDROITIN SULFATE (BOVINE); Glucosamine sulfate; GLYCYRRHIZA GLABRA; CARBOMER 1342; PHENOXYETHANOL; CASSIA FISTULA FRUIT; ETHYLHEXYLGLYCERIN

Hot Spot Point Relief

ACTIVE INGREDIENT

acitve ingredients: capsaicin

INACTIVE INGREDIENT

aqua (deionized water), carbomer, cassia oil, choldroitin sulfate, ethylhexylglycerine, glucosamine sulfate, glycrrhiza glabra (licorice) extract, phenoxyethanol, polysorbate-20

keep out of reach of children. if swallowed consult physician.

WARNINGS

for external use only

avoid contact with eyes

do not apply to open wounds or damaged skin

if symptoms persist for more than seven days, discontinue use and consult physician

keep out of reach of children. if swallowed, consult physician.

do not bandage tightly

PURPOSE

external analesic

INDICATIONS AND USAGE

for temprorary relief of minor aches and pains of the muscles and joints associated with simple backache, arthritis, bruises, strains and/or sprains.

DOSAGE AND ADMINISTRATION

apply directly to affected area. do not use more than four times per day.